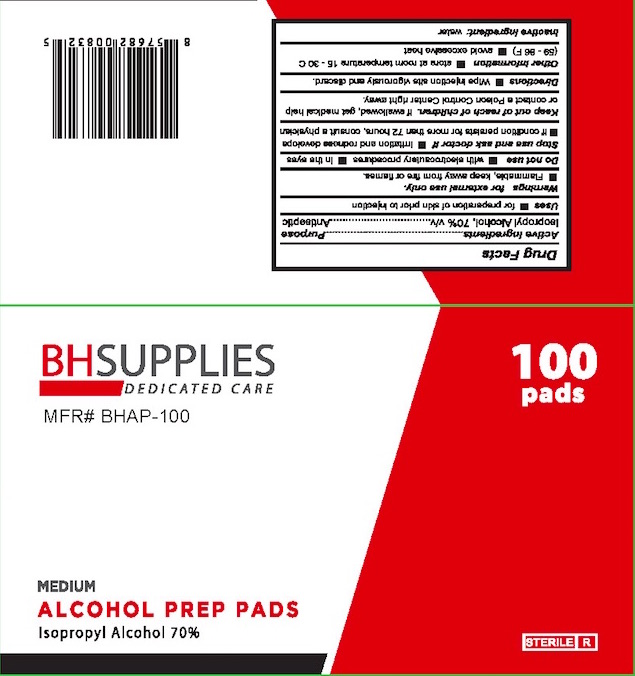 DRUG LABEL: BH SUPPLIES
NDC: 79611-111 | Form: SWAB
Manufacturer: Anrel distribution LLC
Category: otc | Type: HUMAN OTC DRUG LABEL
Date: 20210119

ACTIVE INGREDIENTS: ISOPROPYL ALCOHOL 0.7 mL/1 mL
INACTIVE INGREDIENTS: WATER

Anrel Alcohol pad

Active Ingredient(s)

Isopropyl Alcohol 70% v/v. Purpose: Antiseptic

Purpose

Antiseptic

Use

for preparation of skin prior to injection

Warnings

For external use only. Flammable. Keep away from fire or flame

Do not use

With electrocautery procedures

In the eyes

When using this product keep out of eyes, ears, and mouth. In case of contact with eyes, rinse eyes thoroughly with water.
Stop use and ask a doctor if irritation or rash occurs. These may be signs of a serious condition.
Keep out of reach of children. If swallowed, get medical help or contact a Poison Control Center right away.

STOP USE

If irritation and redness develops

In condition persists for more than 72 hours, consult a physician

Keep out of reach of children. If swallowed, get medical help or contact a Poison Control Center right away.

Directions

Wipe injection area vigorously and discard

Other information

Store at room temperature 15-30 C (59-86 F)

Avoid excessive heat

Inactive ingredients

water

Package Label - Principal Display Panel

100 PCS NDC: 79611-111-11